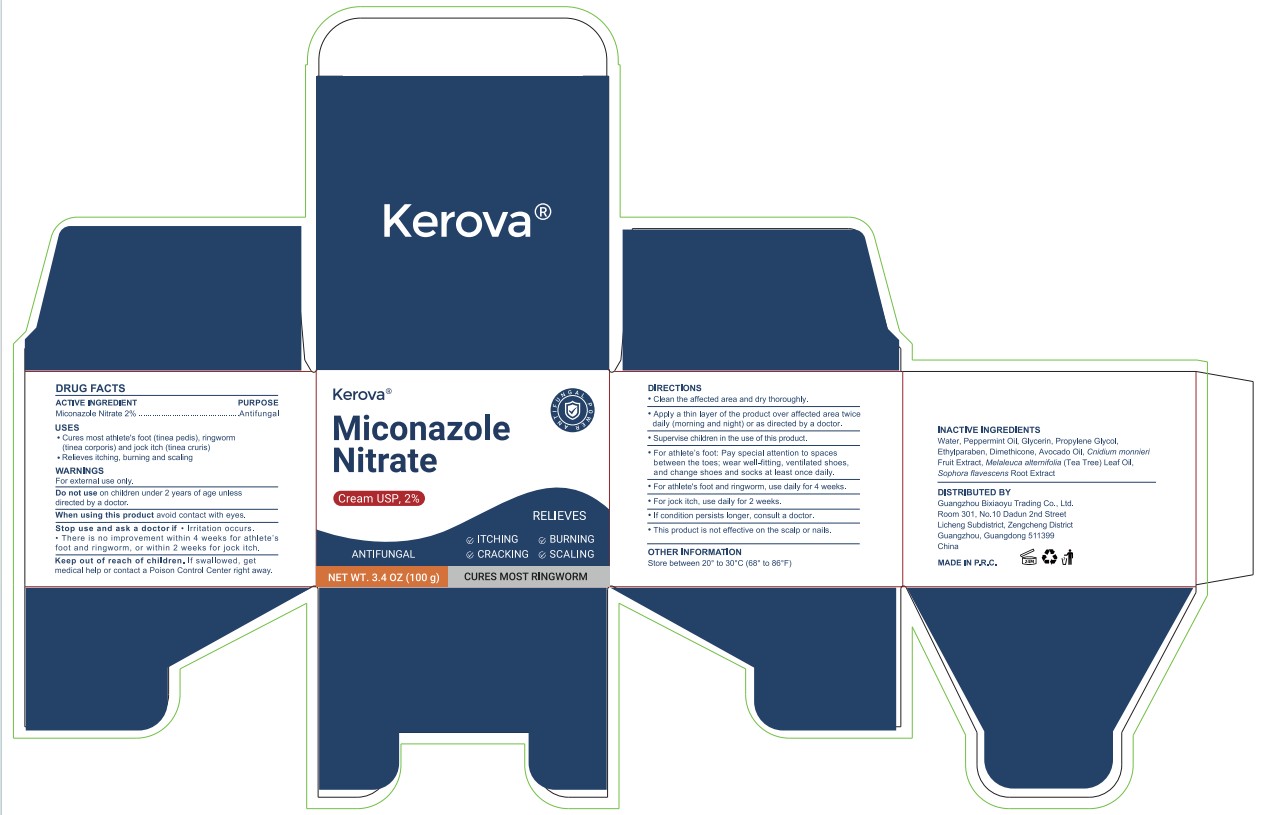 DRUG LABEL: Kerova Miconazole Nitrate
NDC: 85959-001 | Form: CREAM
Manufacturer: Guangzhou Bixiaoyu Trading Co., Ltd.
Category: otc | Type: HUMAN OTC DRUG LABEL
Date: 20260212

ACTIVE INGREDIENTS: MICONAZOLE NITRATE 2 g/100 g
INACTIVE INGREDIENTS: ETHYLPARABEN; AVOCADO OIL; CNIDIUM MONNIERI FRUIT; WATER; PEPPERMINT OIL; DIMETHICONE; MELALEUCA ALTERNIFOLIA (TEA TREE) LEAF OIL; PROPYLENE GLYCOL; SOPHORA FLAVESCENS ROOT; GLYCERIN

ACTIVE INGREDIENT

Miconazole Nitrate 2% Antifungal

PURPOSE

Cures most athlete's foot (tinea pedis),

ringworm(tinea corporis) and jock itch (tinea cruris),

Relieves itching, burning and scaling

DIRECTIONS
"Clean the affected area and dry thoroughly.
*Apply a thin layer of the product over affected area twicedaily (morning and night) or as directed by a doctor.
Supervise children in the use of this product.
"For athlete's foot: Pay special attention to spacesbetween the toes; wear wellfitting, ventilated shoes,and change shoes and socks at least once daily.
For athlete's foot and ringworm, use daily for 4 weeks.
For jock itch, use daily for 2 weeks.
*If condition persists longer, consult a doctor.
.This product is not effective on the scalp or nails.

INACTIVE INGREDIENT

Water, Peppermint Oil, Glycerin, Propylene Glycol,
Ethylparaben, Dimethicone, Avocado Oil, Cnidium monnieri
Fruit Extract, Melaleuca alternifolia (Tea Tree) Leaf Oil,
Sophora flavescens Root Extract

Keep out of reach of children.lf swallowed, getmedical help or contact a Poison Control Center right away.

Stop use and ask a doctorif ,lrritation occurs.

"There is no improvement within 4 weeks for athlete'sfoot and ringworm, or within 2 weeks for jock itch.

WARNINGS

For external use only.

OTHER INFORMATION

Store between 20° to 30°C (68° to 86°F)

Do not use on children under 2 years of age unlessdirected by a doctor.

WARNINGS

For external use only

DOSAGE AND ADMINISTRATION

"For athlete's foot and ringworm, use daily for 4 weeks.
For jock itch, use daily for 2 weeks.
’If condition persists longer, consult a doctor.